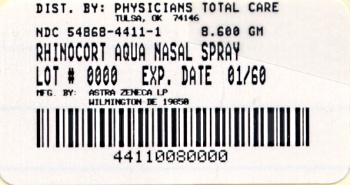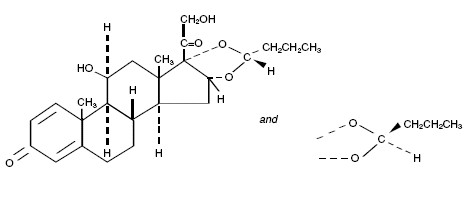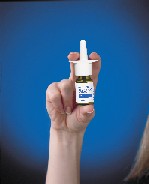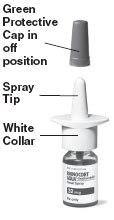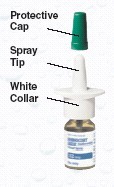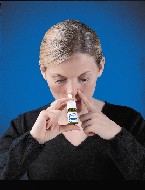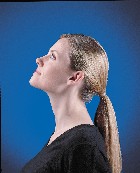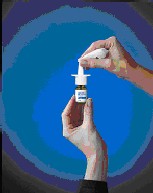 DRUG LABEL: RHINOCORT AQUA
NDC: 54868-4411 | Form: SPRAY, METERED
Manufacturer: Physicians Total Care, Inc.
Category: prescription | Type: HUMAN PRESCRIPTION DRUG LABEL
Date: 20120207

ACTIVE INGREDIENTS: BUDESONIDE 32 ug/1 1
INACTIVE INGREDIENTS: CELLULOSE, MICROCRYSTALLINE; CARBOXYMETHYLCELLULOSE SODIUM; ANHYDROUS DEXTROSE; POLYSORBATE 80; EDETATE DISODIUM; POTASSIUM SORBATE; WATER; HYDROCHLORIC ACID

HIGHLIGHTS OF PRESCRIBING INFORMATION

These highlights do not include all the information needed to use RHINOCORT AQUA® Nasal Spray safely and effectively. See full prescribing information for RHINOCORT AQUA Nasal Spray.
RHINOCORT AQUA 32 mcg (budesonide) Nasal Spray.
INITIAL U.S. APPROVAL: 1999

1 INDICATIONS AND USAGE

RHINOCORT AQUA Nasal Spray is a corticosteroid indicated for:

· Treatment of seasonal or perennial allergic rhinitis in adults and children ≥ 6 years. (1.1)

2 DOSAGE AND ADMINISTRATION

For intranasal use only.

Starting dosage:

· Adult and children 6 years of age and older: 64 mcg (one spray per nostril) once daily. (2)

Maximum dosages:

· Adults 12 years of age and older: 256 mcg (four sprays per nostril) once daily. (2)

· Pediatric patients (6 to <12 years of age): 128 mcg (two sprays per nostril) once daily. (2)

3 DOSAGE FORMS and STRENGTHS

Nasal Spray: 32 mcg budesonide in each metered spray. (3)

Supplied in 8.6 g bottle providing 120 metered sprays after initial priming. (16)

4 CONTRAINDICATIONS

Hypersensitivity to ingredients. (4)

5 WARNINGS AND PRECAUTIONS

· Local Nasal Effects: Epistaxis, Candida albicans infections, nasal septal perforation, impaired wound healing. Monitor patients periodically for signs of adverse effects on the nasal mucosa. Avoid use in patients with recent nasal ulcers, nasal surgery, or nasal trauma. (5.1)

· Hypersensitivity reactions: Anaphylaxis, urticaria, rash, dermatitis, angioedema and pruritus may occur after administration of RHINOCORT AQUA Nasal Spray. (5.2)

· Immunosuppression: Potential worsening of infections (e.g., existing tuberculosis, fungal bacterial, viral, or parasitic infections; or ocular herpes simplex). Use with caution in patients with these infections. More serious or even a fatal course of chickenpox or measles can occur in susceptible patients. (5.3)

· Hypercorticism and adrenal suppression: May occur with very high dosages or at the regular dose in susceptible individuals. If such changes occur, reduce treatment with RHINOCORT AQUA Nasal Spray slowly. (5.4)

· Effect on growth: Monitor growth of pediatric patients. (5.6)

· Glaucoma and cataracts: Close monitoring is warranted. (5.7)

6 ADVERSE REACTIONS

· Most common adverse reactions (incidence ≥ 2%): epistaxis, pharyngitis, bronchospasm, coughing, nasal irritation. (6.1)

To report SUSPECTED ADVERSE REACTIONS, contact AstraZeneca at 1–800–236–9933 or FDA at 1-800-FDA-1088 or www.fda.gov/medwatch.

7 DRUG INTERACTIONS

· Strong cytochrome P450 3A4 inhibitors (e.g., itraconazole, etc,): Use with caution. May cause increased systemic corticosteroid effects. (5.6, 7.1, 12.3)

FULL PRESCRIBING INFORMATION

1 INDICATIONS AND USAGE

1.1 Treatment of Seasonal or Perennial Allergic Rhinitis

RHINOCORT AQUA Nasal Spray is indicated for the treatment of nasal symptoms of seasonal or perennial allergic rhinitis in adults and children six years of age and older.

2 DOSAGE AND ADMINISTRATION

The recommended starting dosage for adults and children 6 years of age and older is 64 mcg per day administered as one spray per nostril of RHINOCORT AQUA Nasal Spray 32 mcg once daily. Some patients who do not achieve symptom control at the recommended starting dosage may benefit from an increased dosage. The maximum recommended dosage for adults (12 years of age and older) is 256 mcg per day administered as four sprays per nostril once daily of RHINOCORT AQUA Nasal Spray 32 mcg and the maximum recommended dose for pediatric patients (6 to <12 years of age) is 128 mcg per day administered as two sprays per nostril once daily of RHINOCORT AQUA Nasal Spray 32 mcg.

It is always desirable to titrate an individual patient to the minimum effective dosage to reduce the possibility of side effects. An improvement in nasal symptoms may be noted in patients within 10 hours of first using RHINOCORT AQUA Nasal Spray, however, clinical improvement usually takes 1-2 days with maximum benefit in approximately 2 weeks. When the maximum benefit has been achieved and symptoms have been controlled, reducing the dosage may be effective in maintaining control of the allergic rhinitis symptoms in patients who were initially controlled on higher dosages.

Prior to initial use, the container must be shaken gently and the pump must be primed by actuating eight times. If used daily, the pump does not need to be reprimed. If not used for two consecutive days, reprime with one spray or until a fine spray appears. If not used for more than 14 days, rinse the applicator and reprime with two sprays or until a fine spray appears. Shake the container gently before each use.

Illustrated Patient’s Instructions for Use accompany each package of RHINOCORT AQUA 32 mcg.

3 DOSAGE FORMS and STRENGTHS

RHINOCORT AQUA Nasal Spray is a nasal spray suspension. Each spray delivers 32 mcg of budesonide. Each bottle of RHINOCORT AQUA Nasal Spray 32 mcg contains 120 metered sprays after initial priming.

4 CONTRAINDICATIONS

RHINOCORT AQUA Nasal Spray is contraindicated in patients with hypersensitivity to any of its ingredients [see Warnings and Precautions (5.2)].

5 WARNINGS AND PRECAUTIONS

5.1 Local Nasal Effects

Epistaxis

In clinical studies of 3 to 52 weeks’ duration epistaxis was observed more frequently in patients treated with RHINOCORT AQUA Nasal Spray than those who received placebo [see Adverse Reactions (6.1)].

Candida Infection

In clinical studies with budesonide administered intranasally, the development of localized infections of the nose and pharynx with Candida albicans has occurred. When such an infection develops, it may require treatment with appropriate local or systemic therapy and discontinuation of treatment with RHINOCORT AQUA Nasal Spray. Patients using RHINOCORT AQUA Nasal Spray over several months or longer should be examined periodically for evidence of Candida infection or other signs of adverse effects on the nasal mucosa.

Nasal Septal Perforation

Instances of nasal septum perforation have been reported following the intranasal application of corticosteroids, including budesonide [see Adverse Reactions (6.2)].

Impaired Wound Healing

Because of the inhibitory effect of corticosteroids on wound healing, patients who have experienced recent nasal septal ulcers, nasal surgery, or nasal trauma should not use a nasal corticosteroid until healing has occurred.

5.2 Hypersensitivity Reactions Including Anaphylaxis

Hypersensitivity reactions including anaphylactic reaction, urticaria, rash, dermatitis, angioedema and pruritus may occur [see Contraindications (4) and Adverse Reactions, Post-marketing Experience (6.2)].

5.3 Immunosuppression

Patients who are on drugs that suppress the immune system are more susceptible to infections than healthy individuals. Chicken pox and measles, for example, can have a more serious or even fatal course in susceptible children or adults using corticosteroids. In such children or adults who have not had these diseases or been properly immunized, particular care should be taken to avoid exposure. How the dose, route, and duration of corticosteroid administration affect the risk of developing a disseminated infection is not known. The contribution of the underlying disease and/or prior corticosteroid treatment to the risk is also not known. If exposed to chicken pox, therapy with varicella zoster immune globulin (VZIG) or pooled intravenous immunoglobulin (IVIG), as appropriate, may be indicated. If exposed to measles, prophylaxis with pooled intramuscular immunoglobulin (IG) may be indicated. (See the respective package inserts for complete VZIG and IG prescribing information). If chicken pox develops, treatment with antiviral agents may be considered.

The clinical course of chicken pox or measles infection in patients on intranasal or inhaled corticosteroids has not been studied. While there is no data with intranasal corticosteroids, a clinical study has examined the immune responsiveness to the varicella vaccine in asthma patients 12 months to 8 years of age who were treated with budesonide inhalation suspension.

An open-label, nonrandomized clinical study examined the immune responsiveness to varicella vaccine in 243 asthma patients 12 months to 8 years of age who were treated with budesonide inhalation suspension 0.25 mg to 1 mg daily (n=151) or non-corticosteroid asthma therapy (n=92) (i.e., beta2-agonists, leukotriene receptor antagonists, or cromones). The percentage of patients developing a seroprotective antibody titer ≥ 5.0 (gpELISA value) in response to the vaccination was similar in patients treated with budesonide inhalation suspension (85%) compared to patients treated with non-corticosteroids asthma therapy (90%). No patient treated with budesonide inhalation suspension developed chicken pox as a result of vaccination.

Corticosteroids should be used with caution, if at all, in patients with active or quiescent tuberculosis infection, untreated fungal, bacterial, systemic viral or parasitic infections; or ocular herpes simplex.

5.4 Hypothalamic-Pituitary-Adrenal Axis Effects

Hypercorticism and Adrenal Suppression: When intranasal steroids are used at higher than recommended dosages or in susceptible individuals at recommended dosages, systemic corticosteroid effects such as hypercorticism and adrenal suppression may appear. If such changes occur, the dosage of RHINOCORT AQUA Nasal Spray should be discontinued slowly, consistent with accepted procedures for discontinuing oral corticosteroid therapy.

The replacement of a systemic corticosteroid with a topical corticosteroid can be accompanied by signs of adrenal insufficiency, and in addition some patients may experience symptoms of corticosteroid withdrawal, e.g., joint and/or muscular pain, fatigue, weakness, nausea, vomiting, hypotension, lassitude, and depression. Patients previously treated for prolonged periods with systemic corticosteroids should be weaned off slowly when transferred to topical corticosteroids and carefully monitored for acute adrenal insufficiency in response to stress. In those patients who have asthma or other clinical conditions requiring long-term systemic corticosteroid treatment, too rapid a decrease in systemic corticosteroids may cause a severe exacerbation of their symptoms.

5.5 Interactions with Strong Cytochrome P450 3A4 Inhibitors

Caution should be exercised when considering the co-administration of RHINOCORT AQUA Nasal Spray with ketoconazole and other known strong CYP3A4 inhibitors (e.g., ritonavir, atazanavir, clarithromycin, indinavir, itraconazole, nefazodone, nelfinavir, saquinavir, telithromycin) because adverse effects related to increased systemic exposure to budesonide may occur [see Drug Interactions (7.1), Clinical Pharmacology (12.3)].

5.6 Effect on Growth

Intranasal corticosteroids, including budesonide may cause a reduction in growth velocity when administered to pediatric patients. Monitor the growth routinely of pediatric patients receiving long-term treatment with RHINOCORT AQUA Nasal Spray. To minimize the systemic effects of intranasal corticosteroids, including RHINOCORT AQUA Nasal Spray, titrate each patient’s dosage to the lowest one that effectively controls his/her symptoms [see Use in Specific Populations, Pediatric Use (8.4)].

5.7 Glaucoma and Cataracts

Glaucoma, increased intraocular pressure and cataracts have been reported following the intranasal application of corticosteroids, including budesonide. Therefore, close monitoring is warranted in patients with a change in vision or with a history of increased intraocular pressure, glaucoma, and/or cataracts [see Adverse Reactions (6.2)].

6 ADVERSE REACTIONS

Systemic and intranasal corticosteroids use may result in the following:

· EpistaxisCandida albicans infection, nasal septum perforation, and impaired wound healing [see Warnings and Precautions (5.1)].

· Hypersensitivity Including Anaphylaxis [see Warnings and Precautions (5.2)].

· Immunosuppression [see Warnings and Precautions (5.3)].

· Hypercorticism and Adrenal Suppression [see Warnings and Precautions (5.4)].

· Growth Effect [see Warnings and Precautions (5.6) and Use in Specific Populations (8.4)].

· Glaucoma and Cataracts [see Warnings and Precautions (5.7)].

6.1 Clinical Trials Experience

Because clinical trials are conducted under widely varying conditions, adverse reaction rates observed in the clinical trials of a drug cannot be directly compared to rates in the clinical trials of another drug and may not reflect the rates observed in practice.

The incidence of common adverse reactions in Table 1 is based upon two U.S. and five non-U.S. controlled clinical trials in 1,526 patients with seasonal or perennial rhinitis in adults and children ≥ 6 years treated with RHINOCORT AQUA Nasal Spray at doses up to 400 mcg once daily for 3-6 weeks. This population included 745 females and 781 males with a mean age of 31 years (range of 6-85 years, 349 were 6 < 18 years). The racial distribution of patients receiving RHINOCORT AQUA Nasal Spray was 93% white, 3% black and 4% other. Table 1 describes adverse reactions occurring at an incidence of 2% or greater and more commonly among RHINOCORT AQUA Nasal Spray-treated patients than in placebo-treated patients in controlled clinical trials.

Table 1. Adverse Reactions occurring at an incidence ≥ 2% and more commonly than placebo in the RHINOCORT AQUA Nasal Spray group in patients 6 years and older
Adverse Event | RHINOCORT AQUA Nasal Spray | Placebo Vehicle
Epistaxis | 8% | 5%
Pharyngitis | 4% | 3%
Bronchospasm | 2% | 1%
Coughing | 2% | <1%
Nasal Irritation | 2% | <1%

A similar adverse reaction profile was observed in the subgroup of pediatric patients 6 to 12 years of age. These patients are included in Table 1.

Two to three percent (2-3%) of patients in clinical trials discontinued because of adverse reactions. Systemic corticosteroid side effects were not reported during controlled clinical studies with RHINOCORT AQUA Nasal Spray.

If recommended doses are exceeded, or if individuals are particularly sensitive, symptoms of hypercorticism, ie, Cushing’s Syndrome, and adrenal suppression could occur.

6.2 Post-marketing Experience

The following adverse reactions have been reported during post-approval use of RHINOCORT AQUA Nasal Spray. Because these reactions are reported voluntarily from a population of uncertain size, it is not always possible to reliably estimate their frequency or establish a causal relationship to drug exposure.

Immune system disorders: immediate and delayed hypersensitivity reactions (including anaphylactic reaction, urticaria, rash, dermatitis, angioedema and pruritus), [see Warnings and Precautions (5.2) and Contraindications (4)]

Eye disorders: glaucoma, increased intraocular pressure, cataracts [see Warnings and Precautions (5.7)]

Respiratory, thoracic, and mediastinal disorders: nasal septum perforation, anosmia, pharynx disorders (throat irritation, throat pain, swollen throat, burning throat, and itchy throat), and wheezing

Cardiac disorders: palpitations

Musculoskeletal and connective tissue disorders: growth suppression [see Warnings and Precautions (5.6) and Use in Specific Populations (8.4)]

7 DRUG INTERACTIONS

7.1 Inhibitors of Cytochrome P450 3A4

The main route of metabolism of corticosteroids, including budesonide, is via cytochrome P450 (CYP) isoenzyme 3A4 (CYP3A4). After oral administration of ketoconazole, a strong inhibitor of CYP3A4, the mean plasma concentration of orally administered budesonide increased. Concomitant administration of CYP3A4 may inhibit the metabolism of, and increase the systemic exposure to, budesonide. Caution should be exercised when considering the co-administration of RHINOCORT AQUA Nasal Spray with long-term ketoconazole and other known strong CYP3A4 inhibitors (e.g., ritonavir, atazanavir, clarithromycin, indinavir, itraconazole, nefazodone, nelfinavir, saquinavir, telithromycin) [see Warnings and Precautions (5.6) and Clinical Pharmacology (12.3)].

8 USE IN SPECIFIC POPULATIONS

8.1 Pregnancy

Teratogenic Effects: Pregnancy Category B. The impact of budesonide on human pregnancy outcomes has been evaluated through assessments of birth registries linked with maternal usage of inhaled budesonide (i.e., PULMICORT TURBUHALER) and intranasally administered budesonide (i.e., RHINOCORT AQUA Nasal Spray). The results from population-based prospective cohort epidemiological studies reviewing data from three Swedish registries covering approximately 99% of the pregnancies from 1995- 2001 (i.e., Swedish Medical Birth Registry; Registry of Congenital Malformations; Child Cardiology Registry) indicate no increased risk for overall congenital malformations from the use of inhaled or intranasal budesonide during early pregnancy.

Congenital malformations were studied in 2,014 infants born to mothers reporting the use of inhaled budesonide for asthma in early pregnancy (usually 10-12 weeks after the last menstrual period), the period when most major organ malformations occur.^1 The rate of overall congenital malformations was similar compared to the general population rate (3.8 % vs. 3.5%, respectively). The number of infants born with orofacial clefts and cardiac defects was similar to the expected number in the general population (4 children vs. 3.3 and 18 children vs. 17-18, respectively). In a follow-on study bringing the total number of infants to 2,534, the rate of overall congenital malformations among infants whose mothers were exposed to inhaled budesonide during early pregnancy was not different from the rate for all newborn babies during the same period (3.6%).^2 A third study from the Swedish Medical Birth Registry of 2,968 pregnancies exposed to inhaled budesonide, the majority of which were first trimester exposures, reported gestational age, birth weight, birth length, stillbirths, and multiple births similar for exposed infants compared to nonexposed infants.^3

Congenital malformations were studied in 2,113 infants born to mothers reporting the use of intranasal budesonide in early pregnancy. The rate of overall congenital malformations was similar compared to the general population rate (4.5% vs. 3.5%, respectively). The adjusted odds ratio (OR) was 1.06 (95% CI 0.86-1.31). The number of infants born with orofacial clefts was similar to the expected number in the general population (3 children vs. 3, respectively). The number of infants born with cardiac defects exceeded that expected in the general population (28 children vs. 17.8 respectively). The systemic exposure from intranasal budesonide is 6-fold less than from inhaled budesonide and an association of cardiac defects was not seen with higher exposures of budesonide.

Despite the animal findings, it would appear that the possibility of fetal harm is remote if the drug is used during pregnancy. Nevertheless, because the studies in humans cannot rule out the possibility of harm, RHINOCORT AQUA Nasal Spray should be used during pregnancy only if clearly needed.

Budesonide produced fetal loss, decreased pup weights, and skeletal abnormalities at a subcutaneous dose in rabbits that was approximately 2 times the maximum recommended daily intranasal dose in adults on a mcg/m^2 basis and at a subcutaneous dose in rats that was approximately 16 times the maximum recommended daily intranasal dose in adults on a mcg/m^2 basis. No teratogenic or embryocidal effects were observed in rats when budesonide was administered by inhalation at doses up to approximately 8 times the maximum recommended daily intranasal dose in adults on a mcg/m^2 basis.

Experience with oral corticosteroids since their introduction in pharmacologic, as opposed to physiologic doses suggests that rodents are more prone to teratogenic effects from corticosteroids than humans.

Nonteratogenic Effects: Hypoadrenalism may occur in infants born of mothers receiving corticosteroids during pregnancy. Such infants should be carefully observed.

8.3 Nursing Mothers

Budesonide is secreted in human milk. Data with budesonide delivered via dry powder inhaler indicates that the total daily oral dose of budesonide available in breast milk to the infant is approximately 0.3% to 1% of the dose inhaled by the mother [see Clinical Pharmacology, Pharmacokinetics, Special Populations, Nursing (12.3)]. No studies have been conducted in breastfeeding women specifically with RHINOCORT AQUA Nasal Spray; however, the dose of budesonide available to the infant in breast milk, as a percentage of the maternal dose, would be expected to be similar. RHINOCORT AQUA Nasal Spray should be used in nursing women only if clinically appropriate. Prescribers should weigh the known benefits of breastfeeding for the mother and infant against the potential risks of minimal budesonide exposure in the infant. Dosing considerations include prescription or titration to the lowest clinically effective dose and use of RHINOCORT AQUA Nasal Spray immediately after breastfeeding to maximize the time interval between dosing and breastfeeding to minimize infant exposure.

8.4 Pediatric Use

Safety and effectiveness in pediatric patients below 6 years of age have not been established.

Controlled clinical studies have shown that intranasal corticosteroids may cause a reduction in growth velocity in pediatric patients. This effect has been observed in the absence of laboratory evidence of hypothalamic-pituitary-adrenal (HPA)-axis suppression, suggesting that growth velocity is a more sensitive indicator of systemic corticosteroid exposure in pediatric patients than some commonly used tests of HPA-axis function. The long-term effects of this reduction in growth velocity associated with intranasal corticosteroids, including the impact on final adult height, are unknown. The potential for "catch-up" growth following discontinuation of treatment with intranasal corticosteroids has not been adequately studied.

The growth of pediatric patients receiving intranasal corticosteroids, including RHINOCORT AQUA Nasal Spray, should be monitored routinely (e.g., via stadiometry). The potential growth effects of prolonged treatment should be weighed against clinical benefits obtained and the risks and benefits associated with alternative therapies. To minimize the systemic effects of intranasal corticosteroids, including RHINOCORT AQUA Nasal Spray, each patient should be titrated to the lowest dose that effectively controls his/her symptoms.

A one-year placebo-controlled clinical growth study was conducted in 229 pediatric patients (ages 4 through 8 years of age) to assess the effect of RHINOCORT AQUA Nasal Spray (single-daily dose of 64 mcg, the recommended starting dose for children ages 6 years and above) on growth velocity. From a population of 141 patients receiving RHINOCORT AQUA Nasal Spray and 67 receiving placebo, the point estimate for growth velocity with RHINOCORT AQUA Nasal Spray was 0.25 cm/year lower than that noted with placebo (95% confidence interval ranging from 0.59 cm/year lower than placebo to 0.08 cm/year higher than placebo).

In a study of asthmatic children 5-12 years of age, those treated with budesonide administered via a dry powder inhaler 200 mcg twice daily (n=311) had a 1.1-centimeter (0.433 inch) reduction in growth compared with those receiving placebo (n=418) at the end of one year; the difference between these two treatment groups did not increase further over three years of additional treatment. By the end of four years, children treated with budesonide dry powder inhaler and children treated with placebo had similar growth velocities. Conclusions drawn from this study may be confounded by the unequal use of corticosteroids in the treatment groups and inclusion of data from patients attaining puberty during the course of the study.

The systemic effects of inhaled corticosteroids are related to the systemic exposure to such drugs. Pharmacokinetic studies have demonstrated that in both adults and children, systemic exposure to budesonide at the highest recommended doses of RHINOCORT AQUA Nasal Spray would be expected to be no greater than exposure at the lowest recommended doses via a dry powder inhaler. Therefore, the systemic effects (HPA axis and growth) of budesonide delivered from RHINOCORT AQUA Nasal Spray would be expected to be no greater than what is reported for inhaled budesonide when administered via the dry powder inhaler.

The potential for RHINOCORT AQUA Nasal Spray to cause growth suppression in susceptible patients or when given at doses above 64 mcg daily cannot be ruled out. The recommended dosage range in patients 6 to 11 years of age is 64 to 128 mcg per day [see Dosage and Administration (2)].

8.5 Geriatric Use

Of the 2,461 patients in clinical studies of RHINOCORT AQUA Nasal Spray, 5% were 60 years of age and over. No overall differences in safety or effectiveness were observed between these subjects and younger subjects, except for an adverse reaction reporting frequency of epistaxis that increased with age. Further, other reported clinical experience has not identified any other differences in responses between elderly and younger patients, but greater sensitivity of some older individuals cannot be ruled out.

8.6 Hepatic Impairment

Formal pharmacokinetic studies using RHINOCORT AQUA Nasal Spray have not been conducted in patients with hepatic impairment. However, since budesonide is predominantly cleared by hepatic metabolism, impairment of liver function may lead to accumulation of budesonide in plasma. Therefore, patients with hepatic disease should be closely monitored.

10 OVERDOSAGE

Acute overdosage with this dosage form is unlikely since one 120 spray bottle of RHINOCORT AQUA Nasal Spray 32 mcg only contains approximately 5.4 mg of budesonide. Chronic overdosage may result in signs/symptoms of hypercorticism [see Warnings and Precautions (5.4)].

11 DESCRIPTION

Budesonide, the active ingredient of RHINOCORT AQUA Nasal Spray, is an anti-inflammatory synthetic corticosteroid.

It is designated chemically as (RS)-11-beta, 16-alpha, 17, 21-tetrahydroxypregna-1,4-diene-3,20-dione cyclic 16, 17-acetal with butyraldehyde.

Budesonide is provided as the mixture of two epimers (22R and 22S).

The empirical formula of budesonide is C25H34O6 and its molecular weight is 430.5.

Its structural formula is:

Budesonide is a white to off-white, odorless powder that is practically insoluble in water and in heptane, sparingly soluble in ethanol, and freely soluble in chloroform.

Its partition coefficient between octanol and water at pH 5 is 1.6 x 10^3.

RHINOCORT AQUA Nasal Spray is an unscented, metered-dose, manual-pump spray formulation containing a micronized suspension of budesonide in an aqueous medium. Microcrystalline cellulose and carboxymethyl cellulose sodium, dextrose anhydrous, polysorbate 80, disodium edetate, potassium sorbate, and purified water are contained in this medium; hydrochloric acid is added to adjust the pH to a target of 4.5.

RHINOCORT AQUA Nasal Spray delivers 32 mcg of budesonide per spray.

Each bottle of RHINOCORT AQUA Nasal Spray 32 mcg contains 120 metered sprays after initial priming.

Prior to initial use, the container must be shaken gently and the pump must be primed by actuating eight times. If used daily, the pump does not need to be reprimed. If not used for two consecutive days, reprime with one spray or until a fine spray appears. If not used for more than 14 days, rinse the applicator and reprime with two sprays or until a fine spray appears.

12 CLINICAL PHARMACOLOGY

12.1 Mechanism of Action

Budesonide is an anti-inflammatory corticosteroid that exhibits potent glucocorticoid activity and weak mineralocorticoid activity. In standard in vitro and animal models, budesonide has approximately a 200-fold higher affinity for the glucocorticoid receptor and a 1000-fold higher topical anti-inflammatory potency than cortisol (rat croton oil ear edema assay). As a measure of systemic activity, budesonide is 40 times more potent than cortisol when administered subcutaneously and 25 times more potent when administered orally in the rat thymus involution assay. The clinical significance of this is unknown.

The activity of RHINOCORT AQUA Nasal Spray is due to the parent drug, budesonide. In glucocorticoid receptor affinity studies, the 22R form was two times as active as the 22S epimer. In vitro studies indicated that the two forms of budesonide do not interconvert.

The precise mechanism of corticosteroid actions on inflammation in seasonal and perennial allergic rhinitis is not well known. Inflammation is an important component in the pathogenesis of seasonal and perennial allergic rhinitis. Corticosteroids have a wide range of inhibitory activities against multiple cell types (e.g., mast cells, eosinophils, neutrophils, macrophages, and lymphocytes) and mediators (e.g., histamine, eicosanoids, leukotrienes, and cytokines) involved in allergic and non-allergic-mediated inflammation. These anti-inflammatory actions of corticosteroids may contribute to their efficacy in seasonal and perennial allergic rhinitis.

12.2 Pharmacodynamics

A 3-week clinical study in seasonal rhinitis, comparing RHINOCORT Nasal Inhaler, orally ingested budesonide, and placebo in 98 patients with allergic rhinitis due to birch pollen, demonstrated that the therapeutic effect of RHINOCORT Nasal Inhaler can be attributed to the topical effects of budesonide.

HPA Axis Effects:

The effects of RHINOCORT AQUA Nasal Spray on adrenal function have been evaluated in several clinical trials. In a four-week clinical trial, 61 adult patients who received 256 mcg daily of RHINOCORT AQUA Nasal Spray demonstrated no significant differences from patients receiving placebo in plasma cortisol levels measured before and 60 minutes after 0.25 mg intramuscular cosyntropin. There were no consistent differences in 24-hour urinary cortisol measurements in patients receiving up to 400 mcg daily. Similar results were seen in a study of 150 children and adolescents aged 6 to 17 with perennial rhinitis who were treated with 256 mcg daily for up to 12 months.

After treatment with the recommended maximal daily dose of RHINOCORT AQUA Nasal Spray (256 mcg) for seven days, there was a small, but statistically significant decrease in the area under the plasma cortisol-time curve over 24 hours (AUC0-24h) in healthy adult volunteers.

A dose-related suppression of 24-hour urinary cortisol excretion was observed after administration of RHINOCORT AQUA Nasal Spray doses ranging from 100-800 mcg daily for up to four days in 78 healthy adult volunteers. The clinical relevance of these results is unknown.

12.3 Pharmacokinetics

Absorption

After intranasal administration of a single dose of RHINOCORT AQUA Nasal Spray (128 mcg), the mean peak plasma concentration of approximately 0.3 nmol/L occurs about 0.5 hours post-dose. Compared to an intravenous dose, approximately 34% of the delivered intranasal dose reaches the systemic circulation, most of which is absorbed through the nasal mucosa. While budesonide is well absorbed from the GI tract, the oral bioavailability of budesonide is low (~10%) primarily due to extensive first pass metabolism in the liver.

Distribution

The volume of distribution of budesonide was approximately 2-3 L/kg. It was 85-90% bound to plasma proteins. The volume of distribution for the 22R epimer is almost twice that of the 22S epimer. Protein binding was constant over a concentration range (1-100 nmol/L) achieved with, and exceeding, recommended doses of RHINOCORT AQUA Nasal Spray. Budesonide showed little or no binding to corticosteroid binding globulin. Budesonide rapidly equilibrated with red blood cells in a concentration independent manner with a blood/plasma ratio of about 0.8.

Metabolism

In vitro studies with human liver homogenates have shown that budesonide is rapidly and extensively metabolized. Two major metabolites formed via cytochrome P450 (CYP) isoenzyme 3A4 (CYP3A4)-catalyzed biotransformation have been isolated and identified as 16α-hydroxyprednisolone and 6β-hydroxybudesonide. The corticosteroid activity of each of these two metabolites is less than 1% of that of the parent compound. No qualitative difference between the in vitro and in vivo metabolic patterns have been detected. Negligible metabolic inactivation was observed in human lung and serum preparations.

Excretion/Elimination

The 22R form of budesonide was preferentially cleared by the liver with systemic clearance of 1.4 L/min vs. 1.0 L/min for the 22S form. The terminal half-life, 2 to 3 hours, was the same for both epimers and was independent of dose. Budesonide was excreted in urine and feces in the form of metabolites. Approximately 2/3 of an intranasal radiolabeled dose was recovered in the urine and the remainder in the feces. No unchanged budesonide was detected in the urine.

Specific Populations

Geriatric

The pharmacokinetics of RHINOCORT AQUA Nasal Spray in geriatric patients have not been specifically studied.

Pediatric

Following administration of RHINOCORT AQUA Nasal Spray, the time to reach peak drug concentrations and plasma half-life were similar in children and in adults. Children had plasma concentrations approximately twice those observed in adults due primarily to differences in weight between children and adults.

Gender

No specific pharmacokinetic study has been conducted to evaluate the effect of gender on budesonide pharmacokinetics. However, following administration of 400 mcg of RHINOCORT AQUA Nasal Spray to 7 male and 8 female volunteers in a pharmacokinetic study, no major gender differences in the pharmacokinetic parameters were found.

Race

No specific study has been undertaken to evaluate the effect of race on budesonide pharmacokinetics.

Nursing Mothers

The disposition of budesonide when delivered by oral inhalation from a dry powder inhaler at doses of 200 or 400 mcg twice daily for at least 3 months was studied in eight lactating women with asthma from 1 to 6 months postpartum. Systemic exposure to budesonide in these women appears to be comparable to that in non-lactating women with asthma from other studies. Breast milk obtained over eight hours post-dose revealed that the maximum concentration of budesonide for the 400 and 800 mcg doses was 0.39 and 0.78 nmol/L, respectively, and occurred within 45 minutes after dosing. The estimated oral daily dose of budesonide from breast milk to the infant was approximately 0.007 and 0.014 mcg/kg/day for the two dose regimens used in this study, which represents approximately 0.3% to 1% of the dose inhaled by the mother. Budesonide levels in plasma samples obtained from five infants at about 90 minutes after breastfeeding (and about 140 minutes after drug administration to the mother) were below quantifiable levels (<0.02 nmol/L in four infants and <0.04 nmol/L in one infant) [see Use in Specific Populations, Nursing Mothers (8.3)].

Renal or Hepatic Impairment

The pharmacokinetics of budesonide have not been investigated in patients with renal impairment. Reduced liver function may affect the elimination of corticosteroids. The pharmacokinetics of budesonide were affected by compromised liver function as evidenced by a doubled systemic availability after oral ingestion. The relevance of this finding to intranasally administered budesonide has not been established.

Drug-Drug Interactions

Inhibitors of cytochrome P450 enzymes

Ketoconazole: Ketoconazole, a strong inhibitor of cytochrome P450 (CYP) isoenzyme 3A4 (CYP3A4), the main metabolic enzyme for corticosteroids, increased plasma levels of orally ingested budesonide [see Warnings and Precautions (5.5) and Drug Interactions (7.1)].

Cimetidine: At recommended doses, cimetidine, a non-specific inhibitor of CYP enzymes, had a slight but clinically insignificant effect on the pharmacokinetics of oral budesonide.

13 NONCLINICAL TOXICOLOGY

13.1Carcinogenesis, Mutagenesis, Impairment of Fertility

In a 104-week oral study in Sprague-Dawley rats, a statistically significant increase in the incidence of gliomas was observed in the male rats receiving an oral dose of budesonide 50 mcg/kg/day (approximately twice the maximum recommended daily intranasal dose in adults and children on a mcg/m^2 basis). No tumorigenicity was seen in male rats at oral doses up to 25 mcg/kg (approximately equal to the maximum recommended daily intranasal dose in adults and children on a mcg/m^2 basis, and in female rats at oral doses up to 50 mcg/kg approximately two times the maximum recommended daily intranasal dose in adults and children on a mcg/m^2 basis). In two additional two-year studies in male Fischer and Sprague-Dawley rats, budesonide caused no gliomas at an oral dose of 50 mcg/kg (approximately twice the maximum recommended daily intranasal dose in adults and children on a mcg/m^2 basis). However, in the male Sprague-Dawley rats, budesonide caused a statistically significant increase in the incidence of hepatocellular tumors at an oral dose of 50 mcg/kg (approximately twice the maximum recommended daily intranasal dose in adults and children on a mcg/m^2 basis). The concurrent reference corticosteroids (prednisolone and triamcinolone acetonide) in these two studies showed similar findings.

There was no evidence of a carcinogenic effect when budesonide was administered orally for 91-weeks to mice at doses up to 200 mcg/kg/day (approximately 3 times the maximum recommended daily intranasal dose in adults and children on a mcg/m^2 basis).

Budesonide was not mutagenic or clastogenic in six different test systems: Ames Salmonella/microsome plate test, mouse micronucleus test, mouse lymphoma test, chromosome aberration test in human lymphocytes, sex-linked recessive lethal test in Drosophila melanogaster, and DNA repair analysis in rat hepatocyte culture.

In rats, budesonide had no effect on fertility at subcutaneous doses up to 80 mcg/kg (approximately 3 times the maximum recommended daily intranasal dose in adults on mcg/m^2 basis).

At a subcutaneous dose of 20 mcg/kg/day (less than the maximum recommended daily intranasal dose in adults on a mcg/m^2 basis), decreases in maternal body weight gain, prenatal viability, and viability of the young at birth and during lactation were observed. No such effects were noted at 5 mcg/kg (less than the maximum recommended daily intranasal dose in adults on a mcg/m^2 basis).

13.2 Animal Toxicology and/or Pharmacology

Budesonide was teratogenic and embryocidal in rabbits and rats. Budesonide produced fetal loss, decreased pup weights, and skeletal abnormalities at a subcutaneous dose of 25 mcg/kg in rabbits (approximately 2 times the maximum recommended daily intranasal dose in adults on a mcg/m^2 basis) and at a subcutaneous dose of 500 mcg/kg in rats (approximately 16 times the maximum recommended daily intranasal dose in adults on a mcg/m^2 basis). No teratogenic or embryocidal effects were observed in rats when budesonide was administered by inhalation doses up to 250 mcg/kg (approximately 8 times the maximum recommended daily intranasal dose in adults on a mcg/m^2 basis).

14 CLINICAL STUDIES

The therapeutic efficacy of RHINOCORT AQUA Nasal Spray has been evaluated in placebo-controlled clinical trials of seasonal and perennial allergic rhinitis of 3-6 weeks duration.

The number of patients treated with budesonide in these studies was 90 males and 51 females aged 6-12 years and 691 males and 694 females 12 years and above. The patients were predominantly Caucasian.

Overall, the results of these clinical trials showed that RHINOCORT AQUA Nasal Spray administered once daily provides statistically significant reduction in the severity of nasal symptoms of seasonal and perennial allergic rhinitis including runny nose, sneezing, and nasal congestion.

An improvement in nasal symptoms may be noted in patients within 10 hours of first using RHINOCORT AQUA Nasal Spray. This time to onset is supported by an environmental exposure unit study in seasonal allergic rhinitis patients that demonstrated that RHINOCORT AQUA Nasal Spray led to a statistically significant improvement in nasal symptoms compared to placebo by 10 hours. Further support comes from a clinical study of patients with perennial allergic rhinitis which demonstrated a statistically significant improvement in nasal symptoms for both RHINOCORT AQUA Nasal Spray and for the active comparator (mometasone furoate) compared to placebo by 8 hours. Onset was also assessed in this study with peak nasal inspiratory flow rate and this endpoint failed to show efficacy for either active treatment. Although statistically significant improvements in nasal symptoms compared to placebo were noted within 8-10 hours in these studies, about one half to two thirds of the ultimate clinical improvement with RHINOCORT AQUA Nasal Spray occurs over the first 1-2 days, and maximum benefit may not be achieved until approximately 2 weeks after initiation of treatment.

15 REFERENCES

^1 Kallen B, Rydhstroem H, Aberg A. Congenital malformations after the use of inhaled budesonide in early pregnancy. Obstet Gynecol 1999; 93:392-395.

^2 Ericson A, Kallen B. Use of drugs during pregnancy: unique Swedish registration method that can be improved. Swedish Medical Products Agency 1999;1:8-11.

^3 Norjavaara E, Gerhardsson de Verdier M. Normal pregnancy outcomes in a population-based study including 2968 pregnant women exposed to budesonide. J Allergy Clin Immunol 2003;111:736-742.

16 HOW SUPPLIED/STORAGE AND HANDLING

RHINOCORT AQUA Nasal Spray 32 mcg is available in an amber glass bottle with a metered-dose pump spray and a green protection cap.

RHINOCORT AQUA Nasal Spray 32 mcg (NDC 54868-4411-1) provides 120 metered sprays after initial priming; net fill weight 8.6 g.

The RHINOCORT AQUA Nasal Spray 32 mcg bottle has been filled with an excess to accommodate the priming activity. The bottle should be discarded after 120 sprays following initial priming, since the amount of budesonide delivered per spray thereafter may be substantially less than the labeled dose. Each spray delivers 32 mcg of budesonide to the patient.

RHINOCORT AQUA Nasal Spray should be stored at controlled room temperature, 20 to 25°C (68 to 77°F) with the valve up. Do not freeze. Protect from light. Shake gently before use. Do not spray in eyes.

17 PATIENT COUNSELING INFORMATION

[See FDA-Approved Patient Labeling]

Patients being treated with RHINOCORT AQUA Nasal Spray should receive the following information and instructions. This information is intended to aid the patient in the safe and effective use of the medication. It is not a disclosure of all possible adverse or intended effects. For proper use of RHINOCORT AQUA Nasal Spray and to attain maximum improvement, the patient should read and follow the accompanying FDA Approved Patient Labeling.

17.1 Local Nasal Effects

Patients should be advised that epistaxis and localized infections with Candida albicans occurred in the nose and pharynx in some patients. If candidiasis develops, it should be treated with appropriate local or systemic therapy and discontinue treatment with RHINOCORT AQUA Nasal spray. In addition, nasal corticosteroids are associated with nasal septal perforation and impaired wound healing. Patients who have experienced recent nasal ulcers, nasal surgery, or nasal trauma should not use RHINOCORT AQUA Nasal Spray until healing has occurred [see Warnings and Precautions (5.1)].

17.2 Hypersensitivity including Anaphylaxis

Patients should be advised that hypersensitivity reactions including anaphylactic reaction, urticaria, rash, dermatitis, angioedema and pruritus have been reported with use of RHINOCORT AQUA Nasal Spray. Discontinue RHINOCORT AQUA Nasal Spray if such reactions occur [see Contraindications (4) Warnings and Preacautions(5.2) and Adverse Reactions (6)].

17.3 Immunosuppression

Patients who are on immunosuppressant doses of corticosteroids should be warned to avoid exposure to chickenpox or measles and, if exposed, to consult their physician without delay. Patients should be informed of potential worsening of existing tuberculosis, fungal, bacterial, viral, or parasitic infection, or ocular herpes simplex [see Warnings and Precautions (5.3)].

17.4 Reduced Growth Velocity

Patients should be advised that intranasal corticosteroids, including budesonide, may cause a reduction in growth velocity when administered to pediatric patients. Physicians should closely follow the growth of children and adolescents taking corticosteroids by any route [see Warnings and Precautions (5.7)].

17.5 Glaucoma and Cataracts

Patients should be advised that long-term use of intranasal corticosteroids, including budesonide, may increase the risk of some eye problems (cataracts and glaucoma). Patients should inform his/her healthcare provider if a change in vision is noted while using RHINOCORT AQUA Nasal Spray [see Warnings and Precautions (5.7)].

17.6 Use Daily

Patients should use RHINOCORT AQUA Nasal Spray at regular intervals since its effectiveness depends on its regular use. Patients may note an improvement in nasal symptoms within 10 hours of first using RHINOCORT AQUA Nasal Spray. Maximum benefit may not be achieved until approximately 2 week after initiation of treatment [see Dosage and Administration (2)].

Patients should take the medication as directed and should not exceed the prescribed dosage. The patient should contact the physician if symptoms do not improve after two weeks, or if the condition worsens. Patients who experience recurrent episodes of epistaxis (nosebleeds) or nasal septum discomfort while taking this medication should contact their physician. For proper use of RHINOCORT AQUA Nasal Spray and to attain maximum improvement, the patient should read and follow the accompanying patient information carefully. Do not use RHINOCORT AQUA Nasal Spray after the labeled number of sprays have been used (does not include priming) or after the expiration date shown on the carton or bottle label.

17.7 How to use RHINOCORT AQUA Nasal Spray

Patients should be carefully instructed on the use of this drug product to assure optimal dose delivery [see Patient Information].

All trademarks are the property of the AstraZeneca group of companies

©AstraZeneca 2008, 2009, 2010

Distributed by:

AstraZeneca LP, Wilmington, DE 19850

Rev. 12/10

Additional barcode labeling by:
Physicians Total Care, Inc.
Tulsa, Oklahoma 74146

Patient Information

RHINOCORT AQUA®

(RINE-o-cort AH-kwa)

(budesonide)

Nasal Spray

For use in your nose only

Read the Patient Information that comes with RHINOCORT AQUA Nasal Spray before you start using it and each time you get a refill. There may be new information. This information does not take the place of talking with your healthcare provider about your medical condition or treatment. If you have questions about RHINOCORT AQUA Nasal Spray, ask your healthcare provider or pharmacist.

What is RHINOCORT AQUA Nasal Spray?

RHINOCORT AQUA Nasal Spray is a prescription medicine used to treat seasonal and year-round allergy symptoms in adults and children 6 years of age and older.

RHINOCORT AQUA Nasal Spray contains budesonide, which is a man-made (synthetic) corticosteroid. Intranasal corticosteroids are natural hormones found in the body that reduce swelling of the lining of your nose. When you spray RHINOCORT AQUA Nasal Spray into your nose, it helps reduce the nasal symptoms of allergic rhinitis (inflammation of the lining of the nose), such as stuffy nose, runny nose, itching and sneezing.

The safety and effectiveness of RHINOCORT AQUA Nasal Spray has not been shown in children under 6 years of age.

Who should not use RHINOCORT AQUA Nasal Spray?

Do not use RHINOCORT AQUA Nasal Spray:

· if you are allergic to budesonide or any of the ingredients in RHINOCORT AQUA Nasal Spray. See the end of this leaflet for a complete list of the ingredients in RHINOCORT AQUA Nasal Spray.

What should I tell my healthcare provider before using RHINOCORT AQUA Nasal Spray?

Before you use RHINOCORT AQUA Nasal Spray, tell your healthcare provider or pharmacist if you:

- have recently been around anyone with chicken pox or measles
- have liver problems
- have any untreated infections
- have ever had an infection called tuberculosis
- have an eye infection
- have recently had surgery or an injury to your nose
- have any other medical conditions
- are pregnant or plan to become pregnant. It is not known if RHINOCORT AQUA Nasal Spray will harm your unborn baby. Talk to your doctor if you are pregnant or plan to become pregnant.
- are breastfeeding or plan to breastfeed. RHINOCORT AQUA Nasal Spray can pass into your breast milk. Talk to your doctor about the best way to feed your baby if you take RHINOCORT AQUA Nasal Spray.

Tell your healthcare provider about all the medicines you take, including prescription and non-prescription medicines, vitamins, and herbal supplements.

RHINOCORT AQUA Nasal Spray may affect the way other medicines work, and other medicines may affect how RHINOCORT AQUA Nasal Spray works.

Know the medicines you take. Keep a list of your medicines with you to show your healthcare provider and pharmacist when you get a new medicine.

How should I use RHINOCORT AQUA Nasal Spray?

- RHINOCORT AQUA Nasal Spray is for use in your nose only. Do not spray it in your eyes or mouth.
- Use RHINOCORT AQUA Nasal Spray exactly as your healthcare provider tells you to use it.
- It is very important that you use RHINOCORT AQUA Nasal Spray regularly. Do not stop using RHINOCORT AQUA Nasal Spray or change your dose without talking to your healthcare provider, even if you are feeling better.
- Talk to your healthcare provider if your symptoms do not improve after taking RHINOCORT AQUA Nasal Spray for 2 weeks or if your symptoms get worse.
- An adult should help a young child use this medicine.
- See the Patient Instructions for Use at the end of this leaflet for complete information on how to use RHINOCORT AQUA Nasal Spray.

What are the possible side effects of RHINOCORT AQUA Nasal Spray?

RHINOCORT AQUA Nasal Spray may cause serious side effects including:

- hole in the cartilage inside the nose (nasal septal perforation). Tell your healthcare provider if you have a whistling sound from your nose when you breathe.
- slow wound healing. You should not use RHINOCORT AQUA Nasal Spray until your nose has healed if you have a sore in your nose, if you have had surgery on your nose, or if your nose has been injured.
- fungal infection in your nose.
- allergic reactions. Tell your healthcare provider or get medical help right away if you have:
- skin rash, redness or swelling
- severe itching
- swelling of the face, mouth and tongue
- immune system problems that may increase your risk of infections. You are more likely to get infections if you take medicines that weaken your body’s ability to fight infections. Avoid contact with people who have contagious diseases such as chicken pox or measles while using RHINOCORT AQUA Nasal Spray. Symptoms of infection may include fever, pain, aches, chills, feeling tired, nausea and vomiting.
- adrenal insufficiency. Adrenal insufficiency is a condition in which the adrenal glands do not make enough steroid hormones. Symptoms of adrenal insufficiency may include tiredness, weakness, nausea, vomiting and low blood pressure.
- slowed or delayed growth in children. A child’s growth should be checked regularly while using RHINOCORT AQUA Nasal Spray.
- eye problems, such as glaucoma and cataracts. Tell your healthcare provider if you have a change in vision or have a history of increased intraocular pressure, glaucoma, and/or cataracts.

Call your healthcare provider or get medical help right away if you have symptoms of any of the serious side effects listed above.

The most common side effects of RHINOCORT AQUA Nasal Spray include:

- nose bleeds
- sore throat
- breathing difficulties such as wheezing, or chest tightening
- cough
- irritation of your nose

Tell your healthcare provider if you have any side effect that bothers you or does not go away.

These are not all of the possible side effects of RHINOCORT AQUA Nasal Spray. For more information, ask your healthcare provider or pharmacist.

Call your healthcare provider for medical advice about side effects. You may report side effects to FDA at 1-800-FDA-1088 or www.fda.gov/medwatch.

You may report side effects to AstraZeneca at 1-800-236-9933.

What should I know about allergic rhinitis?

“Rhinitis” means inflammation of the lining of the nose. It is sometimes called “hay fever.” Allergic rhinitis can be caused by allergies to pollen, animal dander, house dust mite, and mold spores. If you have allergic rhinitis, your nose becomes stuffy, runny, and itchy. You may also sneeze a lot. You may have red, itchy, watery eyes; itchy throat; or blocked, itchy ears.

RHINOCORT AQUA Nasal Spray helps to relieve your nasal symptoms.

If you also have itchy, watery eyes, you should tell your healthcare provider. He or she can prescribe additional medication to treat these symptoms.

How should I store RHINOCORT AQUA Nasal Spray?

- Store RHINOCORT AQUA Nasal Spray at 68°F to 77°F (20°C to 25°C).
- Do not freeze RHINOCORT AQUA Nasal Spray.
- Protect RHINOCORT AQUA Nasal Spray from light.
- Do not use RHINOCORT AQUA Nasal Spray after the labeled number of sprays have been used (does not include priming) or after the expiration date shown on the carton or bottle label.
- Keep the green protective cap on RHINOCORT AQUA Nasal Spray when not in use. (Please see Prior to Use on reverse side).
- Keep RHINOCORT AQUA Nasal Spray and all medications out of the reach of children.

General Information about the safe and effective use of RHINOCORT AQUA Nasal Spray:

Do not use RHINOCORT AQUA Nasal Spray for a condition for which it was not prescribed. Do not give RHINOCORT AQUA Nasal Spray to other people, even if they have the same symptoms that you have. It may harm them.

This Patient Information leaflet summarizes the most important information about RHINOCORT AQUA Nasal Spray. If you would like more information, talk with your healthcare provider. You can ask your pharmacist or healthcare provider for information about RHINOCORT AQUA Nasal Spray that is written for health professionals.

For more information, go to www.astrazenca-us.com or call AstraZeneca at 1-800-236-9933.

What are the Ingredients of RHINOCORT AQUA Nasal Spray?

Active ingredient: budesonide

Inactive ingredients:

Microcrystalline cellulose and carboxymethyl cellulose sodium, dextrose anhydrous, polysorbate 80, disodium edetate, potassium sorbate, purified water and hydrochloric acid.

Patient Instructions for Use

For use in your nose only. Do not spray in your eyes or mouth.

Read the Patient Instructions for Use carefully before you start to use RHINOCORT AQUA Nasal Spray. If you have any questions, ask your healthcare provider.

Figure A

How to prime your RHINOCORT AQUA Nasal Spray

Before you use RHINOCORT AQUA Nasal Spray, the bottle must be primed. To prime RHINOCORT AQUA Nasal Spray:

1. Pull to remove the green protective cap off the nasal spray unit.

2. Shake the bottle gently for a few seconds before each use.

3.Hold the bottle firmly, as shown in Figure B, with your index and middle finger on either side of the spray tip and your thumb underneath the bottle.

Figure B

4. Activate the pump by quickly and firmly pressing down on the white collar while holding the base of the bottle with your thumb.

5. Before your first use of RHINOCORT AQUA Nasal Spray, shake the bottle gently. The pump must be primed by pressing down on the white collar 8 times. The pump is now ready to use. If used daily the pump does not need to be reprimed. If not used for 2 days in a row, reprime with 1 spray or until a fine spray appears. If not used for more than 14 days, rinse the spray tip of the pump using the cleaning steps listed at the end of this leaflet. After cleaning reprime with 2 sprays or until a fine spray appears.

Each bottle of RHINOCORT AQUA Nasal Spray contains enough medicine for you to spray medicine from the bottle 120 times after the bottle is primed.

You should not use the bottle of RHINOCORT AQUA Nasal Spray after 120 sprays. Additional sprays after 120 may not contain the right amount of medicine. You should keep track of the number of sprays you use from each bottle of RHINOCORT AQUA Nasal Spray and throw away any remaining medicine that may be left in the bottle. Refill your prescription monthly.

How to use your RHINOCORT AQUA Nasal Spray

Follow these instructions for daily use of RHINOCORT AQUA Nasal Spray:

1. Gently blow your nose to clear your nostrils, if necessary.

2. Shake the bottle gently for a few seconds and remove the green protective cap.

3. Hold the bottle firmly with your index and middle finger on either side of the spray tip and your thumb underneath the bottle (See Figure C).

Figure C

4. Insert the spray tip into your nostril (the tip should not reach far into your nose). Close the other nostril with a finger and lean your head slightly forward so the spray will aim toward the back of your nose (See Figure D).

Figure D

5. For each spray, activate the pump by quickly and firmly pressing down on the white collar while holding the base of the bottle with your thumb. Breathe gently inward through the nostril.

6. After spraying into your nostril, lean your head backward for a few seconds (Figure E).

Figure E

7. If a second spray is needed in the same nostril, repeat steps 3 through 6.

8. Repeat steps 3 through 7 for your other nostril.

9. Avoid blowing your nose for 15 minutes after you use RHINOCORT AQUA Nasal Spray.

10. Wipe the spray tip with a clean tissue (Figure F), and replace the green protective cap. Store the bottle in an upright position.

Figure F

How to clean your RHINOORT AQUA Nasal Spray

Figure G

Rinse the green protective cap and the spray tip regularly. To do this:

1. Remove the green protective cap and lift off the spray tip (See Figure G).

2. Wash only the green protective cap and the spray tip in warm water and rinse them in cold tap water.

3. Allow the green protective cap and the spray tip to air-dry completely before reassembling the nasal spray.

4.If the spray tip becomes blocked, it can be cleared by repeating Steps 1 through 3. Do not unblock the nasal applicator with a pin or other sharp object.

For additional information about RHINOCORT AQUA® Nasal Spray, please call the AstraZeneca Information Center, Monday through Friday, 8 am – 6 pm ET, excluding holidays at 1-800-236-9933.

All trademarks are the property of the AstraZeneca group of companies

©AstraZeneca 2008, 2009, 2010

Distributed by:

AstraZeneca LP, Wilmington, DE 19850

Rev. 12/10